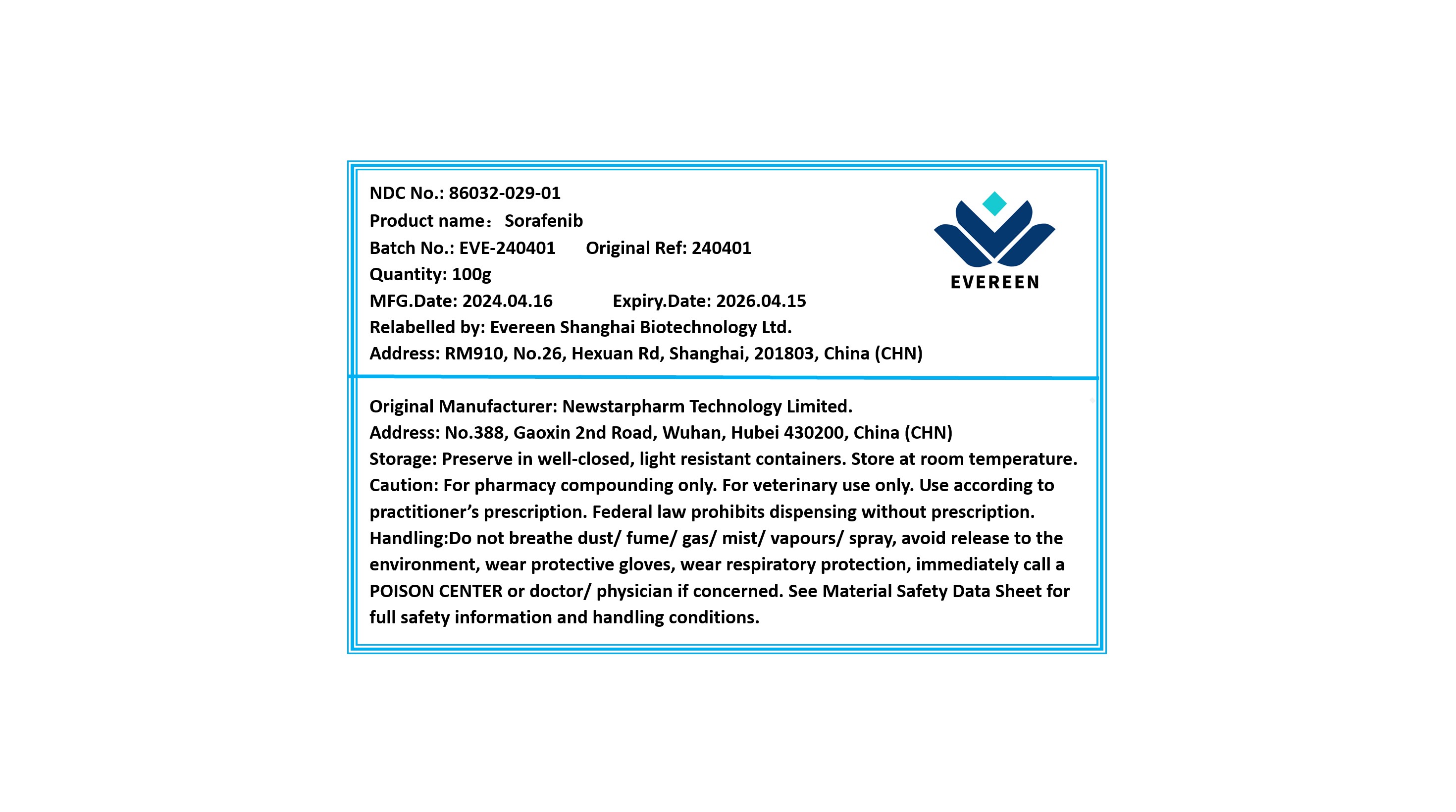 DRUG LABEL: Sorafenib
NDC: 86032-029 | Form: POWDER
Manufacturer: Evereen Shanghai Biotechnology Ltd.
Category: other | Type: BULK INGREDIENT - ANIMAL DRUG
Date: 20240904

ACTIVE INGREDIENTS: SORAFENIB 1 g/1 g

Sorafenib